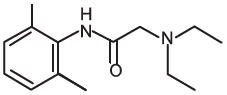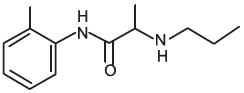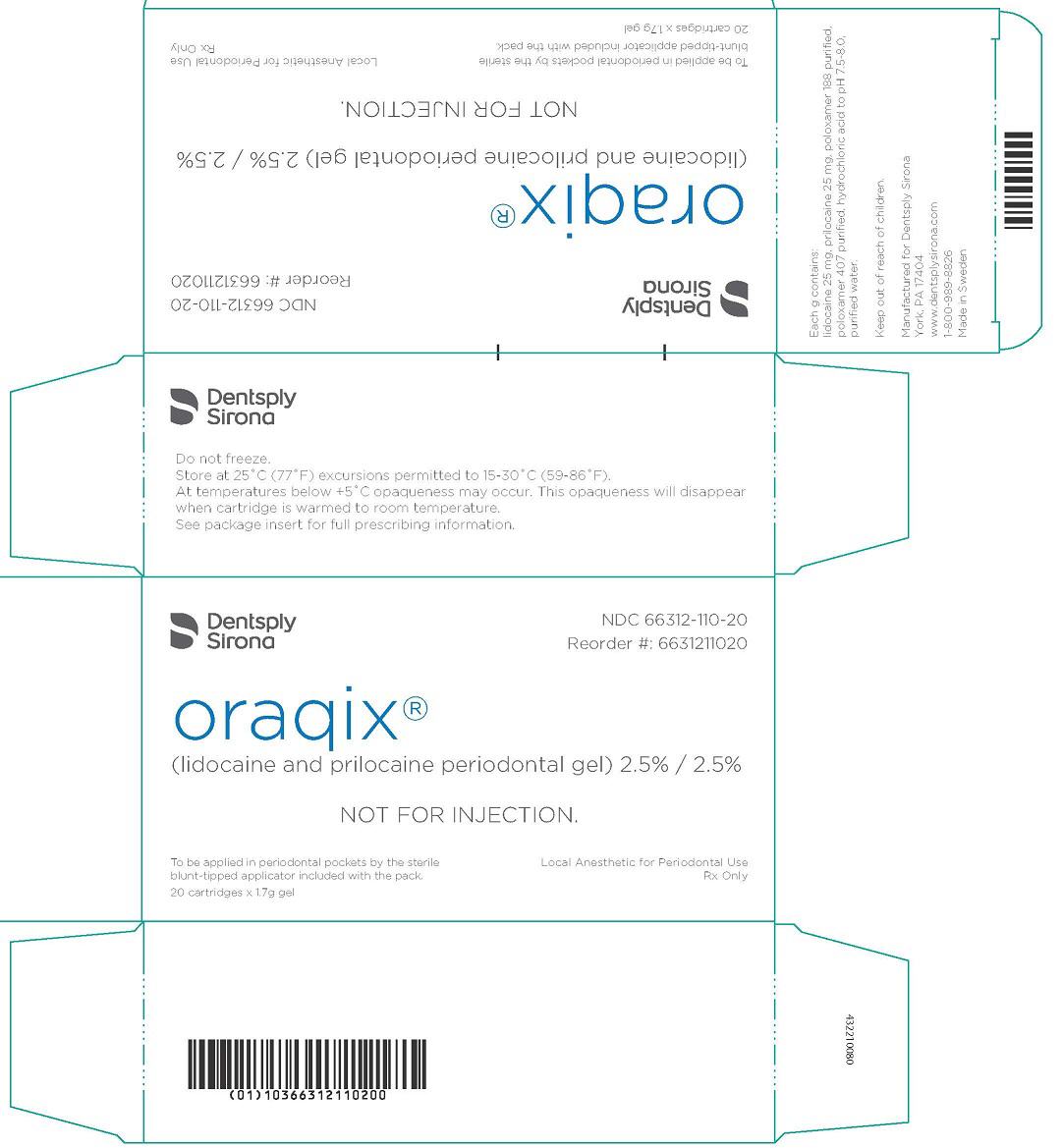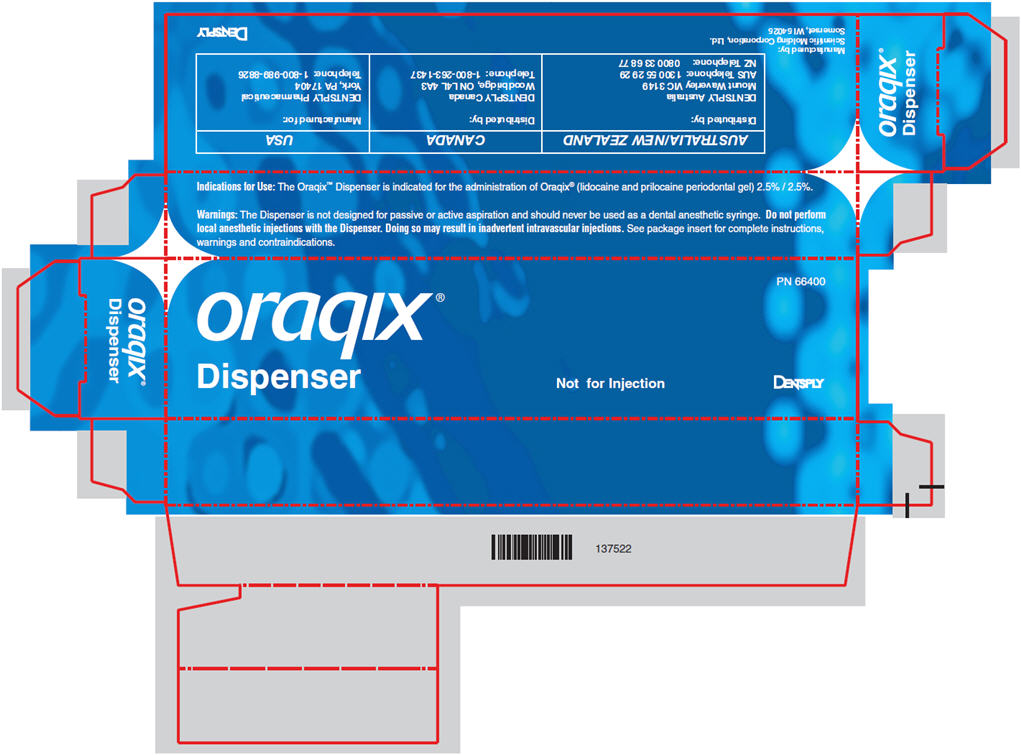 DRUG LABEL: Oraqix
NDC: 66312-110 | Form: GEL
Manufacturer: Dentsply Pharmaceutical
Category: prescription | Type: HUMAN PRESCRIPTION DRUG LABEL
Date: 20240126

ACTIVE INGREDIENTS: LIDOCAINE 25 mg/1 g; PRILOCAINE 25 mg/1 g
INACTIVE INGREDIENTS: POLOXAMER 188; POLOXAMER 407; HYDROCHLORIC ACID; WATER

HIGHLIGHTS OF PRESCRIBING INFORMATION

These highlights do not include all the information needed to use ORAQIX safely and effectively. See full prescribing information for ORAQIX.
ORAQIX® (lidocaine and prilocaine periodontal gel) 2.5%/2.5% Initial U.S. Approval: 2003

RECENT MAJOR CHANGES

Warnings and Precautions, Methemoglobinemia (5.1)

1 INDICATIONS AND USAGE

Oraqix is an amide local anesthetic indicated for adults who require localized anesthesia in periodontal pockets during scaling and/or root planing. (1)

2 DOSAGE AND ADMINISTRATION

- Use the included blunt-tipped applicator and the dispenser, which is sold separately, to apply gel to gingival margins and periodontal pockets. (2)
- May be reapplied as needed up to a maximum of 5 cartridges per treatment session.(2)

3 DOSAGE FORMS AND STRENGTHS

Periodontal gel containing: lidocaine 25 mg/mL and prilocaine 25 mg/mL. (3)

4 CONTRAINDICATIONS

- A history of hypersensitivity to local anesthetics of the amide type (4)
- A history of hypersensitivity to any component of the product (4)

5 WARNINGS AND PRECAUTIONS

- Methemoglobinemia: Cases of methemoglobinemia have been reported in association with local anesthetic use. (5.1)
- DO NOT INJECT (5.2)
- Allergic and anaphylactic reactions can occur (5.3)
- Avoid contact with eyes (5.4)
- Use with caution in patients with severe hepatic disease (5.6)

6 ADVERSE REACTIONS

Most common adverse reactions (incidence >15%) are application site reactions including pain, soreness, irritation, numbness, ulcerations, vesicles, edema, abscess and/or redness. (6.1)

To report SUSPECTED ADVERSE REACTIONS, contact DENTSPLY Pharmaceutical at 1-800-989- 8826 or FDA at 1-800-FDA-1088 or www.fda.gov/medwatch

7 DRUG INTERACTIONS

- Other local anesthetics or agents structurally related to local anesthetics (7.1)
- Drugs That May Cause Methemoglobinemia When Used With ORAQIX (7.2)

8 USE IN SPECIFIC POPULATIONS

- Pregnancy: There have been no adequate and well-controlled studies in pregnant women. Oraqix should be used during pregnancy only if the benefits outweigh the risks. (8.1)
- Nursing Mothers: Exercise caution when administering to a nursing woman. (8.3)
- Pediatric Use: Safety and effectiveness in pediatric patients have not been established. (8.4)

FULL PRESCRIBING INFORMATION

1 INDICATIONS AND USAGE

Oraqix is an amide local anesthetic indicated for adults who require localized anesthesia in periodontal pockets during scaling and/or root planing.

2 DOSAGE AND ADMINISTRATION

2.1 General Dosing Information

DO NOT INJECT [see Warnings and Precautions (5.2)]

Apply Oraqix on the gingival margin around the selected teeth using the blunt-tipped applicator included in the package and the dispenser, which is sold separately. Wait 30 seconds, and then fill the periodontal pockets with Oraqix using the blunt-tipped applicator until the gel becomes visible at the gingival margin. Wait another 30 seconds before starting treatment. A longer waiting time does not enhance the anesthesia. Anesthetic effect, as assessed by probing of pocket depths, has a duration of approximately 20 minutes (individual overall range 14–31 minutes). If the anesthesia starts to wear off, Oraqix may be re-applied if needed. Typically, one cartridge (1.7g) or less of Oraqix will be sufficient for one quadrant of the dentition.

When administered, Oraqix should be a liquid. If it has formed a gel, it should be placed in a refrigerator (do not freeze) until it becomes a liquid again. When in the liquid state, the air bubble visible in the cartridge will move if the cartridge is tilted.

2.2 Maximum Recommended Dosage

The maximum recommended dose of Oraqix at one treatment session is 5 cartridges, i.e., 8.5g gel.

3 DOSAGE FORMS AND STRENGTHS

Periodontal gel containing: lidocaine 25 mg/mL and prilocaine 25 mg/mL. Each cartridge contains 1.7 mL (42.5 mg of lidocaine and 42.5 mg of prilocaine).

4 CONTRAINDICATIONS

Oraqix is contraindicated in patients with a known history of hypersensitivity to local anesthetics of the amide type or to any other component of the product.

5 WARNINGS AND PRECAUTIONS

5.1 Methemoglobinemia

Cases of methemoglobinemia have been reported in association with local anesthetic use. Although all patients are at risk for methemoglobinemia, patients with glucose-6-phosphate dehydrogenase deficiency, congenital or idiopathic methemoglobinemia, cardiac or pulmonary compromise, infants under 6 months of age, and concurrent exposure to oxidizing agents or their metabolites are more susceptible to developing clinical manifestations of the condition. If local anesthetics must be used in these patients, close monitoring for symptoms and signs of methemoglobinemia is recommended.

Signs of methemoglobinemia may occur immediately or may be delayed some hours after exposure and are characterized by a cyanotic skin discoloration and/or abnormal coloration of the blood. Methemoglobin levels may continue to rise; therefore, immediate treatment is required to avert more serious central nervous system and cardiovascular adverse effects, including seizures, coma, arrhythmias, and death. Discontinue ORAQIX and any other oxidizing agents. Depending on the severity of the signs and symptoms, patients may respond to supportive care, i.e., oxygen therapy, hydration. A more severe clinical presentation may require treatment with methylene blue, exchange transfusion, or hyperbaric oxygen.

5.2 DO NOT INJECT

Oraqix should not be used with standard dental syringes. Only use this product with the Oraqix blunt-tipped applicator and the dispenser which is available from DENTSPLY Pharmaceutical.

5.3 Allergic/anaphylactic reactions

Allergic and anaphylactic reactions associated with lidocaine or prilocaine in Oraqix can occur. These reactions may be characterized by urticaria, angioedema, bronchospasm, and shock. If these reactions occur they should be managed by conventional means.

5.4 Avoid Contact with Eyes

Oraqix coming in contact with the eye should be avoided because animal studies have demonstrated severe eye irritation. A loss of protective reflexes may allow corneal irritation and potential abrasion. If eye contact occurs, immediately rinse the eye with water or saline and protect it until normal sensation returns. In addition, the patient should be evaluated by an ophthalmologist, as indicated.

5.5 History of Drug Sensitivity

Patients allergic to paraminobenzoic acid derivatives (procaine, tetracaine, benzocaine, etc.) have not shown cross sensitivity to lidocaine and/or prilocaine. However, Oraqix should be used with caution in patients with a history of drug sensitivities, especially if the etiologic agent is uncertain.

5.6 Severe Hepatic Disease

Patients with severe hepatic disease, because of their inability to metabolize local anesthetics normally, are at greater risk of developing toxic plasma concentrations of lidocaine and prilocaine.

6 ADVERSE REACTIONS

6.1 Clinical Studies Experience

Because clinical trials are conducted under widely varying conditions, adverse reaction rates observed in the clinical trials of a drug can not be directly compared to rates in the clinical trials of another drug and may not reflect the rates observed in practice.

Although no major differences in adverse events between Oraqix and placebo-treated subjects were observed, all patients in the placebo-controlled studies received either Oraqix or a placebo gel (consisting of the vehicle in Oraqix without lidocaine or prilocaine). Therefore, it is not possible to determine if adverse events in each treatment group were attributable to the inactive ingredients comprising the Oraqix or vehicle or if adverse event rates were higher than expected background rates. Therefore, a causal relationship between the reported adverse reactions and Oraqix could neither be established nor ruled out.

Following SRP treatment with Oraqix in 391 patients, the most frequent adverse events were local reactions in the oral cavity (see following table). These events, which occurred in approximately 15% of patients, included pain, soreness, irritation, numbness, vesicles, ulcerations, edema and/or redness in the treated area. Of the 391 patients treated with Oraqix, five developed ulcerative lesions and two developed vesicles of mild to moderate severity near the site of SRP. In addition, ulcerative lesions in or near the treated area were also reported for three out of 168 patients who received placebo. Other symptoms reported in more than one patient were headache, taste perversion, nausea, fatigue, flu, respiratory infection, musculoskeletal pain and accident/injury.

Table 1. Number (percent) of patients with adverse events occurring in more than one patient in any of the treatment groups.
Each patient is counted only once per adverse event. The occurrence in a single patient is included in this table if the same symptom has been seen in at least one patient in another group.
System Organ Class PreferredTerm | Oraqix gel [in a cross-over study, 170 subjects received either Oraqix or lidocaine injection 2% in each test period] (N=391)n (%) | Placebo gel (N=168)n (%) | Lidocaine injection (N=170)n (%)
Muscular-Skeletal System Disorders Myalgia | 1(0) | 2(1)
Arthralgia and/or Arthropathy | 1(0) | 1(1)
Central & Peripheral Nervous System Disorders
Headache | 8(2) | 3(2) | 5(3)
Dizziness | 1(0) | 1(1) | 1(1)
Special Senses Other, Disorders Taste Perversion [includes complaints of bad or bitter taste lasting for up to 4 hours after administration of Oraqix] | 8(2) | 1(1)
Gastro-Intestinal System Disorders Nausea | 3(1) |  | 1(1)
Respiratory System Disorders Respiratory Infection | 2(1) |  | 1(1)
Rhinitis |  | 2(1)
Body as a whole-General Disorders Accident and/or Injury | 2(1) | 2(1)
Fatigue | 3(1) |  | 2(1)
Flu-Like Disorder | 2(1)
Pain (remote from application site) | 1(0) | 1(1) | 1(1)
Application Site Disorders [i.e. symptoms in the oral cavity] Anesthesia Local | 2(1)
Application Site Reaction [includes pain, soreness, irritation, numbness, ulcerations, vesicles, edema, abscess and/or redness in the treated area] | 52(13) | 20(12)

7 DRUG INTERACTIONS

7.1 Other Local Anesthetics or Agents Structurally Related to Local Anesthetics

Oraqix should be used with caution in combination with dental injection anesthesia, other local anesthetics, or agents structurally related to local anesthetics, e.g., Class 1 antiarrhythmics such as tocainide and mexiletine, as the toxic effects of these drugs are likely to be additive and potentially synergistic.

7.2 Drugs That May Cause Methemoglobinemia When Used With ORAQIX

Patients who are administered local anesthetics are at increased risk of developing methemoglobinemia when concurrently exposed to the following drugs, which could include other local anesthetics:

Examples of Drugs Associated with Methemoglobinemia:
Class | Examples
Nitrates/Nitrites | nitric oxide, nitroglycerin, nitroprusside, nitrous oxide
Local anesthetics | articaine, benzocaine, bupivacaine, lidocaine, mepivacaine, prilocaine, procaine, ropivacaine, tetracaine
Antineoplastic agents | cyclophosphamide, flutamide, hydroxyurea, isofamide, rasburicase
Antibiotics | dapsone, nitrofurantoin, para-aminosalicylic acid, sufonamides
Antimalarials | chloroquine, primaquine
Anticonvulsants | Phenobarbital, phenytoin, sodium valproate
Other drugs | acetaminophen, metoclopramide, quinine, sulfasalazine

8 USE IN SPECIFIC POPULATIONS

8.1 Pregnancy

Pregnancy Category B .Reproduction studies have been performed in rats with lidocaine, prilocaine and a 1:1 (weight:weight) mixture of the two compounds. There was no evidence of harm to the fetus at subcutaneous doses of up to 30 mg/kg lidocaine (estimated exposure was approximately equivalent to the expected lidocaine exposure at the maximum recommended human dose of Oraqix (lidocaine and prilocaine periodontal gel) 2.5% / 2.5% on a mg/m^2 basis). Following intramuscular prilocaine doses of up to 300 mg/kg (estimated exposure was approximately 11 times the expected prilocaine exposure at the maximum recommended human dose of Oraqix gel on a mg/m^2 basis), there was no evidence of impaired fertility or harm to the fetus. Similarly, subcutaneous administration of a lidocaine and prilocaine mixture of 40 mg/kg of each compound (estimated exposures were approximately 1.5 times the expected lidocaine and prilocaine exposures at the maximum recommended human dose of Oraqix gel on a mg/m^2 basis) produced no teratogenic, embryotoxic, or fetotoxic effects. Reproductive toxicology studies of lidocaine were also conducted in rabbits. There was no evidence of harm to the fetus at a dose of 5 mg/kg, s.c. (60 mg/m^2). Treatment of rabbits with 15 mg/kg (180 mg/m^2) produced evidence of maternal toxicity and evidence of delayed fetal development, including a non-significant decrease in fetal weight (7%) and an increase in minor skeletal anomalies (skull and sternebral defects, reduced ossification of the phalanges). The effects of lidocaine and prilocaine on post-natal development was examined in rats treated for 8 months with 10 or 30 mg/kg, s.c. lidocaine or prilocaine (60 mg/m^2 and 180 mg/m^2 on a body surface area basis, respectively up to 1.4-fold the maximum recommended exposure for a single procedure). This time period encompassed 3 mating periods. There was no evidence of altered post-natal development in any offspring; however, both doses of either drug reduced the average number of pups per litter surviving until weaning of offspring from the first 2 mating periods. In a separate study, the effect of prilocaine on pre- and postnatal development was examined in rats treated with up to 60 mg/kg, s.c. (up to 2.8 times the maximum recommended human dose of prilocaine in Oraqix gel on a mg/m^2 basis) from Day 6 of gestation to weaning. There was no evidence of altered post-natal development, viability, or reproductive capacity in any offspring. All the above calculations of exposure are assuming 100% bioavailability of lidocaine and prilocaine after Oraqix administration. There are, however, no adequate and well-controlled studies in pregnant women. Because animal reproduction studies are not always predictive of human response, Oraqix should be used during pregnancy only if the benefits outweigh the risks.

Reproduction studies on the Oraqix drug product, including the inactive ingredients, have not been conducted.

8.3 Nursing Mothers

Lidocaine and, possibly, prilocaine are excreted in breast milk. Caution should be exercised when Oraqix is administered to nursing women.

8.4 Pediatric Use

Safety and effectiveness in pediatric patients have not been established. Very young children are more susceptible to methemoglobinemia. There have been reports of clinically significant methemoglobinemia in infants and children following excessive applications of lidocaine 2.5% topical cream [See Warnings and Precautions (5.1)].

8.5 Geriatric Use

Of the total number of subjects in clinical studies of Oraqix, 7% were aged 65 and over, while 1% were aged 75 and over. No overall differences in safety or effectiveness were observed between these subjects and younger subjects. Other reported clinical experience has not identified differences in responses between elderly and younger patients, but greater sensitivity of some older individuals cannot be ruled out.

Dose selection for an elderly patient should be cautious, usually starting at the low end of the dosing range, reflecting the greater frequency of decreased hepatic, renal, or cardiac function, and of concomitant disease or other drug therapy.

10 OVERDOSAGE

10.1 Oraqix/Local anesthetic toxicity emergency

Oraqix used at the recommended doses is not likely to cause toxic plasma levels of lidocaine or prilocaine. However, if other local anesthetics are administered at the same time, e.g. topically or by injection, the toxic effects are thought to be additive and could result in an overdose with systemic toxic reactions. There is generally an increase in severity of symptoms with increasing plasma concentrations of lidocaine and/or prilocaine. Systemic CNS toxicity may occur over a range of plasma concentrations of local anesthetics. CNS toxicity may typically be found around 5000 ng/mL of lidocaine; however a small number of patients reportedly may show signs of toxicity at approximately 1000 ng/mL. Pharmacological thresholds for prilocaine are poorly defined. Central nervous system (CNS) symptoms usually precede cardiovascular manifestations. The plasma level of lidocaine observed after the maximum recommended dose (5 cartridges) of Oraqix in 11 patients exposed over 3 hours ranged from 157 to 552 ng/mL with a mean of 284 ng/mL ± 122 SD. The corresponding figure for prilocaine was 53-181 ng/mL with a mean of 106 ± 45 SD. [See Clinical Pharmacology (12.3)].

Systemic adverse effects of lidocaine and/or prilocaine are manifested by central nervous system and/or cardiovascular symptoms.

Clinical symptoms of systemic toxicity include CNS excitation and/or depression (light-headedness, hyperacusis, visual disturbances, muscular tremors, and general convulsions). Lidocaine and/or prilocaine may cause decreases in cardiac output, total peripheral resistance and mean arterial pressure. These changes may be attributable to direct depressant effects of these local anesthetic agents on the cardiovascular system. Cardiovascular manifestations may include hypotension, bradycardia, arrhythmia, and cardiovascular collapse.

10.2 Management of Oraqix/Local Anesthetic Emergencies

Should severe CNS or cardiovascular symptoms occur, these may be treated symptomatically by, for example, the administration of anticonvulsive drugs, respiratory support and/or cardiovascular resuscitation as necessary.

10.3 Methemoglobinemia

For detailed information on methemoglobinemia causes, symptoms, and treatment, see Warnings and Precautions (5.1).

For additional information about overdose treatment, call a poison control center (1-800-222-1222).

11 DESCRIPTION

Oraqix (lidocaine and prilocaine periodontal gel,) 2.5%/2.5% is a microemulsion in which the oil phase is a eutectic mixture of lidocaine and prilocaine in a ratio of 1:1 by weight. This eutectic mixture has a melting point below room temperature; therefore, both local anesthetics exist as liquid oils rather than as crystals. Oraqix contains poloxamer excipients, which show reversible temperature-dependent gelation. Together with the lidocaine-prilocaine 1:1 mixture, the poloxamers form a low-viscosity fluid system at room temperature and an elastic gel in the periodontal pocket. Oraqix is administered into periodontal pockets, by means of the supplied special applicator. Gelation occurs at body temperature, followed by release of the local anesthetics, lidocaine and prilocaine. The Oraqix single-use glass cartridges deliver up to 1.7g (1.7mL) of gel (42.5 mg of lidocaine and 42.5 mg of prilocaine). Prilocaine base and lidocaine base are both relatively hydrophilic amino-amides.

The structural formulas are:

Lidocaine
C14H22N2O M.W. 234.3

Prilocaine
C13H20N2O M.W. 220.3

Lidocaine is chemically designated as 2-(diethylamino)-N-(2,6-dimethylphenyl)-acetamide and has an octanol:water partition ratio of 43 at pH 7.4. The pKa of lidocaine is 7.86. Prilocaine is chemically designated as N-(2-methyl-phenyl)-2 (propylamino)-propanamide and has an octanol:water partition ratio of 25 at pH 7.4. The pKa of prilocaine is 7.89. Each gram of Oraqix contains 25-mg lidocaine base and 25-mg prilocaine base. The gel also contains thermosetting agents (poloxamer 188 purified, poloxamer 407 purified), hydrochloric acid (pH adjustment), and purified water. The pH of Oraqix is 7.5-8.0.

12 CLINICAL PHARMACOLOGY

12.1 Mechanism of Action

Lidocaine and prilocaine belong to the amide class of local anesthetics. Both lidocaine and prilocaine block sodium ion channels required for the initiation and conduction of neuronal impulses, resulting in local anesthesia.

12.2 Pharmacodynamics

After application of Oraqix on the gingival margin and a waiting period of 30 seconds, additional Oraqix is applied directly into periodontal pockets to provide localized anesthesia. The onset of local anesthetic effect after application of Oraqix into the periodontal pocket occurs by 30 seconds and a longer waiting time does not enhance the anesthetic affect. Anesthetic effect, as assessed by probing of pocket depths, lasted for about 20 minutes (individual overall range 14 to 31 minutes).

12.3 Pharmacokinetics

Absorption: Lidocaine and prilocaine are absorbed from Oraqix via the oral mucous membranes. After a single application of 0.9 to 3.5 g Oraqix, the mean (±SD) lidocaine and prilocaine Cmax values were 182 (±53) and 77 (±27) ng/mL, respectively. After a total of 8 to 8.5 g Oraqix administered as repeated applications over 3 hours, the mean (±SD) lidocaine Cmax was 284 (±122) ng/mL, ranging between 157 and 552 ng/mL. The mean lidocaine AUC∞ was 84,000 ng/min/mL. The mean (±SD) prilocaine Cmax was 106 (±45) ng/mL, ranging between 53 and 181 ng/mL. The mean prilocaine AUC∞ was 26,000 ng/min/mL.

The increase in Cmax of both lidocaine and prilocaine is proportional (or less than proportional) to the dose after single application of Oraqix. The Cmax after a cumulative dose of 8.5 g Oraqix administered as repeated applications over 3 hours, (i.e. the highest recommended dose, corresponding to 212.5 mg each of lidocaine and prilocaine base), is lower than that extrapolated from the proportional increase in plasma concentrations at lower doses.

The median Tmax of lidocaine and prilocaine was 30 minutes, ranging between 20 and 40 min., after the start of a single application of 0.9 to 3.5 g Oraqix, and 200 minutes, ranging between 120 and 200 min., after a cumulative dose of 8.5 g Oraqix administered as repeated applications over 3 hours.

The toxicities of lidocaine and prilocaine are thought to be additive. Systemic CNS toxicity may occur over a range of plasma concentrations of local anesthetics. CNS toxicity may typically be found around 5000 ng/mL of lidocaine, however a small number of patients reportedly may show signs of toxicity at approximately 1000 ng/mL. Pharmacological thresholds for prilocaine are poorly defined.

Distribution: Lidocaine and prilocaine have an intermediate degree of plasma protein binding, mainly to 1-acid glycoprotein, with a protein binding of 70% and 40%, respectively. When administered intravenously, the mean volume of distribution (for 60 kg person) at steady state for lidocaine and prilocaine were 90 L and 156 L, respectively. Oraqix is not intended for intravenous administration. Both lidocaine and prilocaine cross the placental and blood brain barriers, presumably by passive diffusion.

Metabolism: Lidocaine and prilocaine are mainly metabolized in the liver. Prilocaine and lidocaine are not metabolized by plasma esterases. The main metabolism of lidocaine is through N-dealkylation to monoethylglycinexylidide (MEGX) and glycinexylidide (GX), which is mainly mediated by CYP3A4. These metabolites are hydrolyzed to 2,6-xylidine, which is converted to 4-hydroxy- 2,6-xylidine (mediated by CYP2A6), the major urinary metabolite in man. After a total of 8 to 8.5g Oraqix administered as repeated applications over 3 hours, the mean (+SD) 2,6-xylidine Cmax was 18 (+8.4) ng/mL ranging between 8 and 32 ng/mL. The mean 2,6-xylidine AUC∞ was 9800 ng/min/mL (±6370), ranging between 3480 to 24,580 ng/min/mL). MEGX has an antiarrhythmic and convulsant activity similar to that of lidocaine and a somewhat longer half-life. GX has a weak antiarrhythmic effect but lacks convulsant activity and has a half-life of about 10 h.

Prilocaine is split at the amide linkage to o-toluidine, which is converted further to 4- and 6- hydroxytoluidine. The prilocaine metabolite o-toluidine and the hydroxylated metabolites of o-toluidine are excreted mainly in the urine. o-Toluidine has been shown to be carcinogenic in several animal models. After a total of 8 to 8.5g Oraqix was administered as repeated applications over 3 hours, the mean (±SD) o-toluidine Cmax was 25 (±11) ng/mL ranging between 13 and 44 ng/mL. The mean o-toluidine AUC∞ was 9200 ng/min/mL. The median Tmax was 220 minutes, ranging between 90 and 240 min. In addition, o-Toluidine can cause the formation of methemoglobin (metHb) following treatment with prilocaine. Individual maximum blood concentrations of metHb increased from 0 to 1.1% up to 0.8 to 1.7% following administration of the maximum recommended dose of 8.5g Oraqix administrated as repeated applications over 3 hours. The Tmax of metHb ranged from 1 to 4 hours. Normally, <1 % of the total hemoglobin is in the form of metHb. [See OVERDOSAGE (10)]. Patients with glucose-6-phosphate dehydrogenase deficiencies, and patients taking oxidizing drugs such as antimalarials and sulfonamides are more susceptible to drug-induced methemoglobinemia. [See Warnings and Precautions (5.1)].

Elimination: Lidocaine and prilocaine have systemic clearances of 0.95 and 2.37 L/min, respectively, after intravenous administration as single agents. The terminal half-life of both drugs after intravenous administration as single agents is 1.6 h. Oraqix is not intended for intravenous administration.

However, after application of Oraqix to the periodontal pockets the mean (±SD) terminal lidocaine half-life was 3.6 (±1.3)hours, ranging between 2.2 and 6.5 h. The mean (±SD) terminal prilocaine half-life was 2.8 (±1.0) hours, ranging between 2.0 to 5.7 h. For the metabolite o-toluidine the mean terminal half-life was 4.0 (±1.1) hours, ranging between 2.0 and 5.7 hours. For the metabolite 2,6-xylidine the mean terminal half-life was 8.0 (±4.0) hours, ranging between 3.7 and 18.3 hours.

Pediatrics: The pharmacokinetics of lidocaine and prilocaine after Oraqix administration have not been studied in pediatric patients.

Geriatrics: The pharmacokinetics of lidocaine and prilocaine after Oraqix administration have not been studied in geriatric patients. However, intravenous studies, the elimination half-life of lidocaine was statistically significantly longer in elderly patients (2.5 hours) than in younger patients (1.5 hours). No studies in the intravenous pharmacokinetics of prilocaine in elderly patients have been performed.

Special populations: No pharmacokinetic studies were conducted to specifically address special populations.

Renal Impairment: Lidocaine and prilocaine and their metabolites are known to be excreted by the kidney, and the metabolites may accumulate in patients with impaired renal function.

Hepatic Impairment: The half-life of lidocaine may be prolonged two-fold or more in patients with liver dysfunction. Liver dysfunction may also alter prilocaine pharmacokinetics. Because of their inability to metabolize local anesthetics normally, patients with severe hepatic disease, are at a greater risk of developing toxic plasma concentrations of lidocaine and prilocaine.

13 NONCLINICAL TOXICOLOGY

13.1 Carcinogenesis, Mutagenesis, Impairment of Fertility

Carcinogenesis - Long-term studies in animals have not been performed to evaluate the carcinogenic potential of either lidocaine or prilocaine. Chronic oral toxicity studies of o-toluidine, a metabolite of prilocaine, have shown that this compound is a carcinogen in both mice and rats. The tumors associated with o-toluidine included hepatocarcinomas/adenomas in female mice, multiple occurrences of hemangiosarcomas/hemangiomas in both sexes of mice, sarcomas of multiple organs, transitional-cell carcinomas/papillomas of urinary bladder in both sexes of rats, subcutaneous fibromas/fibrosarcomas and mesotheliomas in male rats, and mammary gland fibroadenomas/adenomas in female rats. These findings were observed at the lowest tested dose of 150 mg/kg/day or greater over two years (estimated daily exposures in mice and rats were approximately 6 and 12 times, respectively, the estimated exposure to o-toluidine at the maximum recommended human dose of 8.5g of Oraqix gel on a mg/m^2 basis). Thus, the no effect dose is less than 6 to 12 times the estimated exposure to o-toluidine at the maximum recommended human dose, assuming 100% bioavailability of prilocaine from the Oraqix gel. Complete conversion of prilocaine to its metabolite o-toluidine on a molar basis is assumed. This gives a conversion on a weight basis of about 50% for prilocaine base (dependent on the molecular weights, i.e. 220 for prilocaine base and 107 for o-toluidine).

Mutagenesis - The mutagenic potentials of lidocaine and prilocaine have been tested in the Ames Salmonella reverse mutation assay, an in vitro chromosome aberrations assay in human lymphocytes and in an in vivo mouse micronucleus assay. There was no indication of any mutagenic effects for either compound in these studies. o-Toluidine, metabolite of prilocaine, was positive in Escherichia coli DNA repair and phage-induction assays. Urine concentrates from rats treated orally with 300 mg/kg o-toluidine were mutagenic to Salmonella typhimurium in the presence of metabolic activation. Several other tests on o-toluidine, including reverse mutations in five different Salmonella typhimurium strains with or without metabolic activation, and single strand breaks in DNA of V79 Chinese hamster cells, were negative.

Impairment of Fertility: The effect of lidocaine on fertility was examined in the rat model. Administration of 30 mg/kg, s.c. (180 mg/m^2 or 1.4-fold the maximum recommended human oral dose for one treatment session assuming 100% bioavailability of lidocaine) to the mating pair did not produce alterations in fertility or general reproductive performance of rats. There are no studies that examine the effect of lidocaine or prilocaine on sperm parameters. The effects of prilocaine on fertility was examined in rats treated for 8 months with 10 or 30 mg/kg, s.c. lidocaine or prilocaine (60 mg/m^2 and 180 mg/m^2 on a body surface area basis, respectively up to 1.4-fold the maximum recommended exposure for a single procedure assuming 100% bioavailability of lidocaine and prilocaine). This time period encompassed 3 mating periods. There was no evidence of altered fertility.

14 CLINICAL STUDIES

A total of 337 patients (146 men and 191 women; 169 Oraqix and 168 placebo) were studied in three randomized, double-blind, placebo-controlled trials. Patients received a median dose of approximately 1 cartridge (1.7g gel), ranging from ¼ to 2½ cartridges per quadrant treated. The analgesic effect of Oraqix was assessed by asking patients to rate their pain on a continuous visual analog scale (VAS) from 0 (no pain) to 100 mm (worst pain imaginable). Patients were asked to report overall procedural pain 5 minutes following manual scaling and/or root planing (SRP) in a single quadrant that had been pre-treated with Oraqix or placebo (vehicle only, without lidocaine or prilocaine). In all three studies, patients were given Oraqix or placebo (vehicle only, without lidocaine or prilocaine). In all three studies, patients who were given Oraqix reported lower VAS scores during the procedure than those given placebo. Study B3 recruited patients with a known sensitivity to mechanical probing of dental pockets, whereas in studies B1 and B2, this was not a requirement. Results of B1, B2 and B3 are summarized below.

Table 2. Visual Analog Pain Scale (100 mm scale)
Visual Analog Pain Scale
Study (No. of patients) | Oraqix Median VAS | Placebo Median VAS
B1 (n=122) [p<0.05] | 7 | 17
B2 (n=130) | 5 | 13
B3 (n=85) | 11 | 27

The trial also compared individual patient estimates of pain on a 5-step categorical Verbal Rating Scale (VRS) which included the following categories: no pain, mild pain, moderate pain, severe pain, and very severe pain. The results of those who reported no pain or mild pain are shown in the test table.

Table 3. Verbal Rating Scale
Number of Patients Reporting "no pain" or "mild pain" during SRP
Study (No. of patients) | Oraqix Median VAS | Placebo Median VAS
B1 (n=122) [p<0.05 in the statistical test of the full five categorical scale] | 57 (90%) | 38 (64%)
B2 (n=130) | 49 (78%) | 51 (76%)
B3 (n=85) | 30 (70%) | 20 (48%)

16 HOW SUPPLIED/STORAGE AND HANDLING

Oraqix (lidocaine and prilocaine periodontal gel), 2.5%/2.5%, is supplied in dental cartridges that provide 1.7g gel. Individually blister-packaged cartridges of Oraqix are distributed in a carton of 20 (NDC 66312-110-20). Each individual blister package also contains a sterile blunt-tipped applicator. Each blunt-tipped applicator is for single use only. Oraqix is intended for use with the Oraqix Dispenser.

STORAGE AND HANDLING

Store at 20° to 25°C (68° to 77°F); excursions permitted between 15° to 30°C (59° to 86°F) [see USP Controlled Room Temperature]. [See USP Controlled Room Temperature.] At temperatures below +5°C Oraqix may become opaque. This opacity will disappear when the cartridge is warmed to room temperature.

DO NOT FREEZE. Some components of Oraqix may precipitate if cartridges are frozen. Cartridges should not be used if they contain a precipitate.

Do not use dental cartridge warmers with Oraqix. The heat will cause the product to gel.

See FDA-approved patient labeling (Patient Information)

17 PATIENT COUNSELING INFORMATION

Inform patients that use of local anesthetics may cause methemoglobinemia, a serious condition that must be treated promptly. Advise patients or caregivers to seek immediate medical attention if they or someone in their care experience the following signs or symptoms: pale, gray, or blue colored skin (cyanosis); headache; rapid heart rate; shortness of breath; lightheadedness; or fatigue.

Patients should be cautioned to avoid injury to the treated area, or exposure to extreme hot or cold temperatures, until complete sensation has returned.

Manufactured for:
Dentsply Pharmaceutical
York, PA 17404